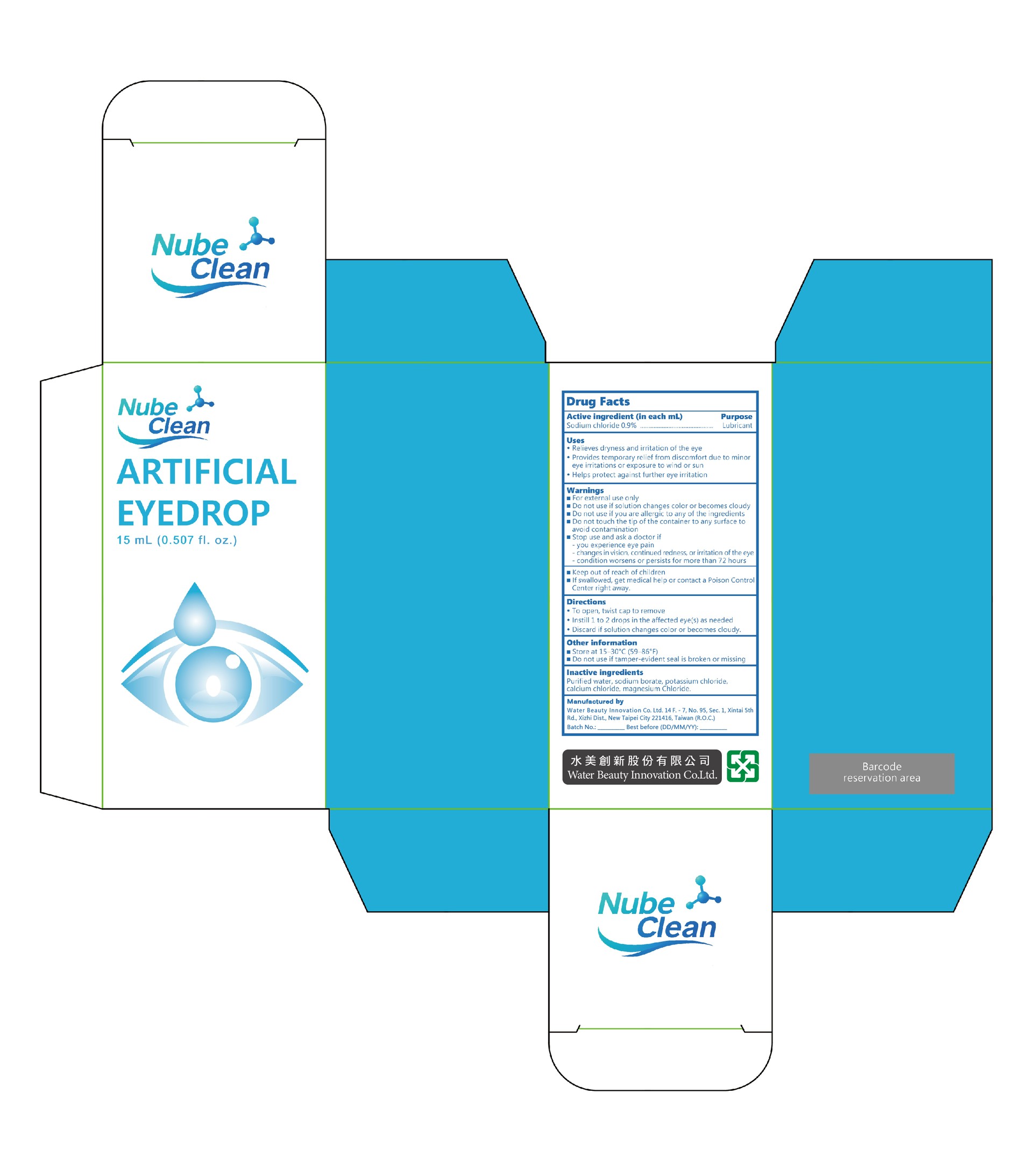 DRUG LABEL: ARTIFICIAL EYEDROP
NDC: 87406-003 | Form: LIQUID
Manufacturer: Water Beauty Innovation Co. Ltd.
Category: otc | Type: HUMAN OTC DRUG LABEL
Date: 20260213

ACTIVE INGREDIENTS: SODIUM CHLORIDE 9 mg/1 mL
INACTIVE INGREDIENTS: SODIUM BORATE; POTASSIUM CHLORIDE; CALCIUM CHLORIDE; WATER; MAGNESIUM CHLORIDE

Water Beauty 003-01

ACTIVE INGREDIENT

Sodium chloride 0.9%

PURPOSE

Lubricant

INDICATIONS AND USAGE

• Relieves dryness and irritation of the eye
• Provides temporary relief from discomfort due to minor eye irritations or exposure to wind or sun
• Helps protect against further eye irritation

WARNINGS

• For external use only

• Do not touch the tip of the container to any surface to avoid contamination

• If swallowed, get medical help or contact a Poison Control Center right away

DO NOT USE

if solution changes color or becomes cloudy
if you are allergic to any of the ingredients

STOP USE

and ask a doctor if

– you experience eye pain
– changes in vision, continued redness, or irritation of the eye
– condition worsens or persists for more than 72 hours

• Keep out of reach of children

DOSAGE AND ADMINISTRATION

• To open, twist cap to remove
• Instill 1 to 2 drops in the affected eye(s) as needed
• Discard if solution changes color or becomes cloudy

STORAGE AND HANDLING

• Store at 15–30°C (59–86°F)
• Do not use if tamper-evident seal is broken or missing

INACTIVE INGREDIENT

Purified water, sodium borate, potassium chloride, calcium chloride, magnesium chloride